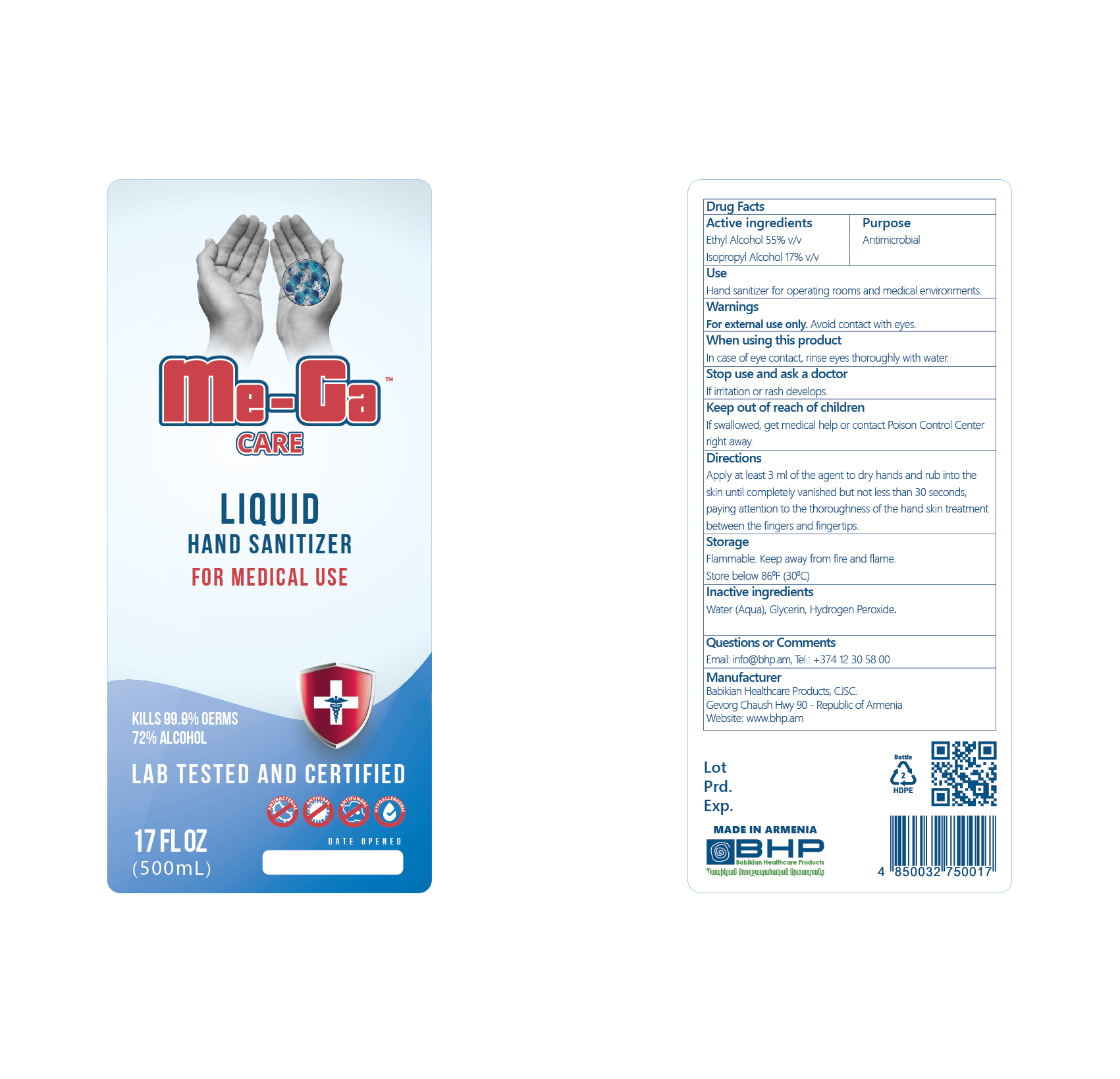 DRUG LABEL: Me-Ga Care
NDC: 83640-272 | Form: LIQUID
Manufacturer: Babikian Healthcare Products CJSC
Category: otc | Type: HUMAN OTC DRUG LABEL
Date: 20250508

ACTIVE INGREDIENTS: ALCOHOL 55 mL/100 mL; ISOPROPYL ALCOHOL 17 mL/100 mL
INACTIVE INGREDIENTS: WATER; GLYCERIN; HYDROGEN PEROXIDE

Drug Facts

Active ingredients................. Purpose

Ethyl Alcohol 55% v/v ...........Antimicrobial

Isopropyl Alcohol 17% v/v......Antimicrobial

Use

Hand sanitizer for operating rooms and medical environments.

Warnings

For external use only. Avoid contact with eyes.

When using this product

In case of eye contact, rinse eyes thoroughly with water.

Stop use and ask a doctor

If irritation or rash develops.

Keep out of reach of children

If swallowed, get medical help or contact Poison Control Center right away.

Directions

Apply at least 3 ml of the agent to dry hands and rub into the skin until completely vanished but not less than 30 seconds, paying attention to the thoroughness of the hand skin treatment between the fingers and fingertips.

Other information

Flammable. Keep away from fire and flame.

Store below 86^0 F (30^0 C).

Inactive ingredients

Water (Aqua), Glycerin, Hydrogen Peroxide.

Questions or Comments

Email: info@bhp.am, Tel.: +374 12 30 58 00

Manufacturer

Babikian Healthcare Products, CJSC.

Gevorg Chaush Hwy 90 - Republic of Armenia

Website: www.bhp.am